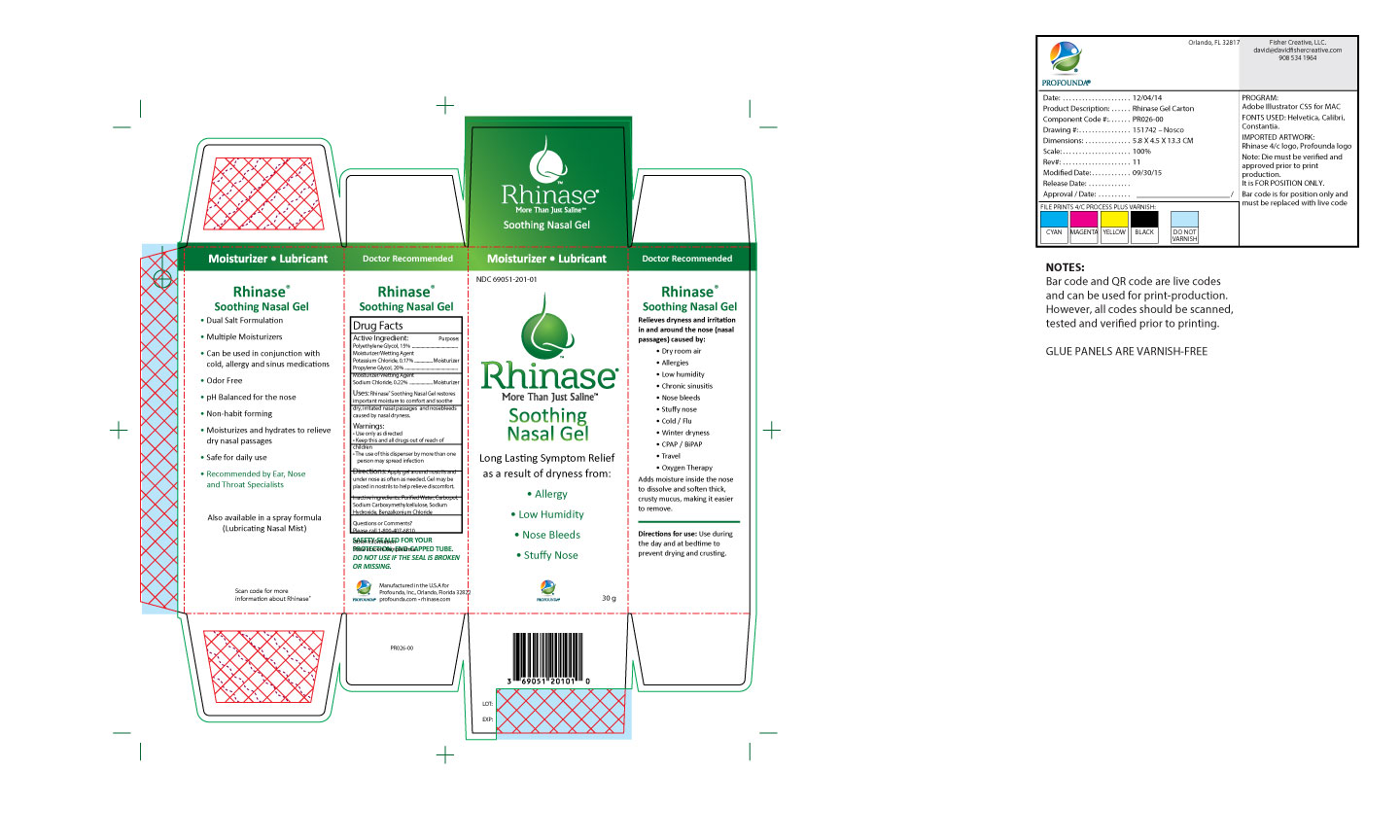 DRUG LABEL: Rhinase Soothing Nasal Gel
NDC: 69051-201 | Form: GEL
Manufacturer: Profounda Inc
Category: otc | Type: HUMAN OTC DRUG LABEL
Date: 20210111

Warnings

- Use only as directed

- Keep this and all drugs out of reach of children

- The use of this dispensor by more than one person may spread infection

Inactive Ingredients

Purified water, Carbopol, Sodium Carboxymethylcellulose, Sodium Hydroxide, Benzalkonium Chloride

Rhinase Soothing Nasal Gel (Side Panel)

Moisturizer / Wetting Agent

Relieves dryness and irritation in and around the nose (nasal passages) caused by: dry room air, allergies, low humidity, chronic sinusitis, nose bleeds, stuffy nose, cold/flu, winter dryness, CPAP/BiPAP, Travel, Oxygen therapy

Adds moisture inside the nose to dissolve and soften thick, crusty mucus, making it easier to remove.

Warnings

Keep this and all drugs out of the reach of children

ACtive Ingredient

Polyethylene Glycol

Potassium Chloride

Propylene Glycol

Sodium Chloride

Directions

Apply gel around nostrils and under nose as often as needed. Gel may be placed in nostrils to help relieve discomfort

Indication and usage

Relieves dryness and irritation to and around the nose (nasal passages) caused by: dry room air, allergies,low humidity, chronic sinusitis, nose bleeds, stuffy nose, cold/flu, winter dryness, CPAP / BiPAP, travel, Oxygen therapy.

Adds moisture inside the nose to dissolve and soften thick, crusty mucus, making it easier to remove.